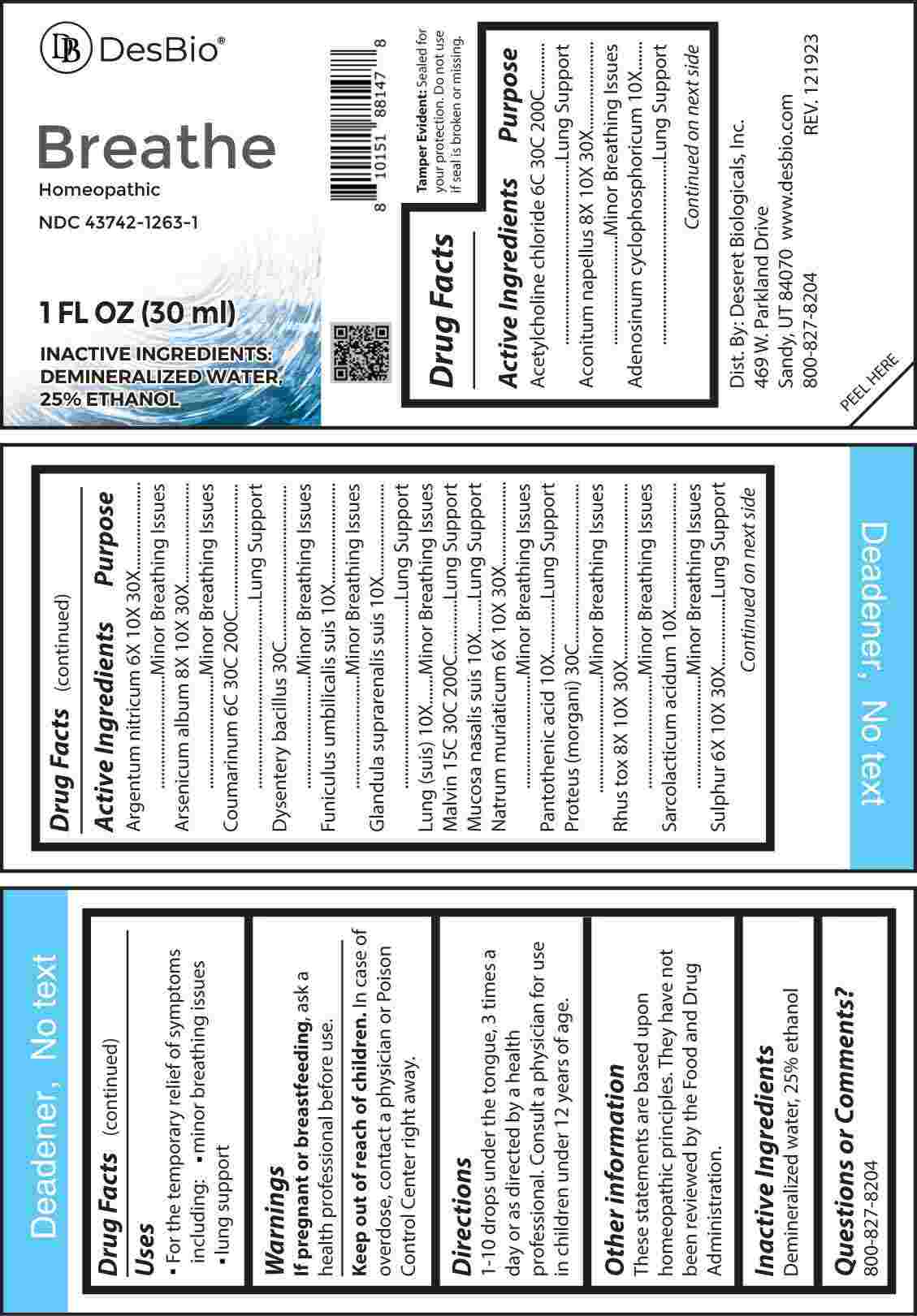 DRUG LABEL: Breathe
NDC: 43742-1263 | Form: LIQUID
Manufacturer: Deseret Biologicals, Inc
Category: homeopathic | Type: HUMAN OTC DRUG LABEL
Date: 20240315

ACTIVE INGREDIENTS: SILVER NITRATE 6 [hp_X]/1 mL; SODIUM CHLORIDE 6 [hp_X]/1 mL; SULFUR 6 [hp_X]/1 mL; ACONITUM NAPELLUS 8 [hp_X]/1 mL; ARSENIC TRIOXIDE 8 [hp_X]/1 mL; TOXICODENDRON PUBESCENS LEAF 8 [hp_X]/1 mL; ADENOSINE CYCLIC PHOSPHATE 10 [hp_X]/1 mL; SUS SCROFA UMBILICAL CORD 10 [hp_X]/1 mL; SUS SCROFA ADRENAL GLAND 10 [hp_X]/1 mL; SUS SCROFA LUNG 10 [hp_X]/1 mL; SUS SCROFA NASAL MUCOSA 10 [hp_X]/1 mL; PANTOTHENIC ACID 10 [hp_X]/1 mL; LACTIC ACID, L- 10 [hp_X]/1 mL; ACETYLCHOLINE CHLORIDE 6 [hp_C]/1 mL; COUMARIN 6 [hp_C]/1 mL; MALVIN 15 [hp_C]/1 mL; SHIGELLA DYSENTERIAE 30 [hp_C]/1 mL; PROTEUS MORGANII 30 [hp_C]/1 mL
INACTIVE INGREDIENTS: WATER; ALCOHOL

DRUG FACTS:

ACTIVE INGREDIENTS:

Acetylcholine Chloride 6C, 30C, 200C, Aconitum Napellus 8X, 10X, 30X, Adenosinum Cyclophosphoricum 10X, Argentum Nitricum 6X, 10X, 30X, Arsenicum Album 8X, 10X, 30X, Coumarinum 6C, 30C, 200C, Dysentery Bacillus 30C, Funiculus Umbilicalis Suis 10X, Glandula Suprarenalis Suis 10X, Lung (Suis) 10X, Malvin 15C, 30C, 200C, Mucosa Nasalis Suis 10, Natrum Muriaticum 6X, 10X, 30X, Pantothenic Acid 10X, Proteus (Morgani) 30C, Rhus Tox 8X, 10X, 30X, Sarcolacticum Acidum 10X, Sulphur 6X, 10X, 30X.

PURPOSE:

Acetylcholine Chloride – Lung Support, Aconitum Napellus – Minor Breathing Issues, Adenosinum Cyclophosphoricum – Lung Support, Argentum Nitricum – Minor Breathing Issues, Arsenicum Album – Minor Breathing Issues, Coumarinum – Lung Support, Dysentery Bacillus – Minor Breathing Issues, Funiculus Umbilicalis Suis – Minor Breathing Issues, Glandula Suprarenalis Suis – Lung Support, Lung (Suis) – Minor Breathing Issues, Malvin – Lung Support, Mucosa Nasalis Suis – Lung Support, Natrum Muriaticum – Minor Breathing Issues, Pantothenic Acid – Lung Support, Proteus (Morgani) – Minor Breathing Issues, Rhus Tox – Minor Breathing Issues, Sarcolacticum Acidum – Minor Breathing Issues, Sulphur – Lung Support

USES:

• For the temporary relief of symptoms including:

• minor breathing issues • lung support

These statements are based upon homeopathic principles. They have not been reviewed by the Food and Drug Administration.

WARNINGS:

If pregnant or breast-feeding, ask a health professional before use.

Keep out of reach of children. In case of overdose, contact a physician or Poison Control Center right away.

Tamper Evident: Sealed for your protection. Do not use if seal is broken or missing.

KEEP OUT OF REACH OF CHILDREN:

In case of overdose, contact a physician or Poison Control Center right away.

DIRECTIONS:

1-10 drops under the tongue, 3 times a day or as directed by a health professional. Consult a physician for use in children under 12 years of age.

INACTIVE INGREDIENTS:

Demineralized water, 25% ethanol

QUESTIONS:

Dist. By: Deseret Biologicals, Inc.
469 W. Parkland Drive
Sandy, UT 84070

www.desbio.com

800-827-8204

PACKAGE LABEL DISPLAY:

Des Bio

Breathe

Homeopathic

NDC 43742-1263-1

1 FL OZ (30 ml)